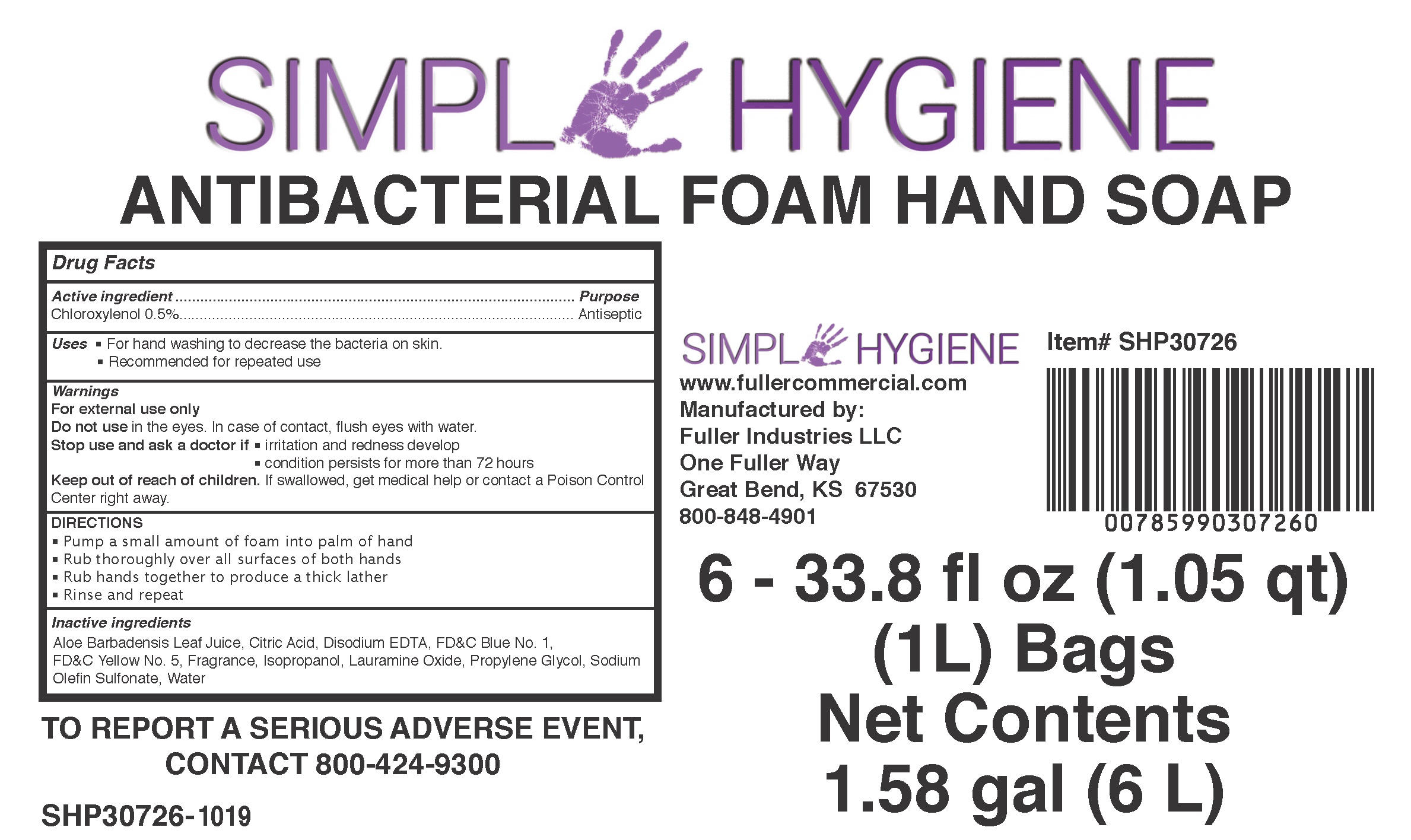 DRUG LABEL: Simple Hygiene Antibacterial Hand
NDC: 60933-210 | Form: AEROSOL, FOAM
Manufacturer: FULLER INDUSTRIES, INC
Category: otc | Type: HUMAN OTC DRUG LABEL
Date: 20231028

ACTIVE INGREDIENTS: CHLOROXYLENOL 5 mg/1 mL
INACTIVE INGREDIENTS: ALOE VERA LEAF; CITRIC ACID MONOHYDRATE; EDETATE DISODIUM ANHYDROUS; FD&C BLUE NO. 1; FD&C YELLOW NO. 5; LAURAMINE OXIDE; WATER; ISOPROPYL ALCOHOL; PROPYLENE GLYCOL

Simple Hygiene Antibacterial Foam Hand Soap

Active ingredient

Chloroxylenol 0.5%

Purpose

Antiseptic

Uses

- For hand washing to decrease the bacteria on skin.
- Recommended for repeated use

Warnings

For external use only

Do not use

in the eyes. In case of contact, flush eyes with water.

Stop use and ask a doctor if

- irritation and redness develop
- condition persists for more than 72 hours

Keep out of reach of children.

If swallowed, get medical help or contact a Poison Control Center right away.

DIRECTIONS

- Pump a small amount of foam into palm of hand
- Rub thoroughly over all surfaces of both hands
- Rub hands together to produce a thick lather
- Rinse and repeat

Inactive ingredients

Aloe Barbadensis Leaf Juice, Citric Acid, Disodium EDTA, FD&C Blue No. 1, FD&C Yellow No. 5, Fragrance, Isopropanol, Lauramine Oxide, Propylene Glycol, Sodium Olefin Sulfonate, Water